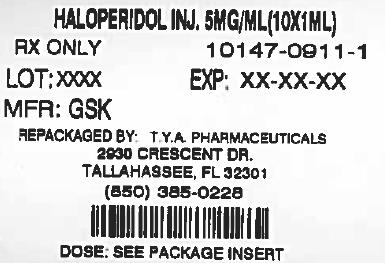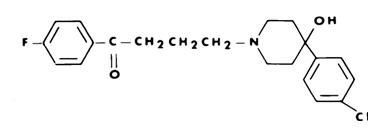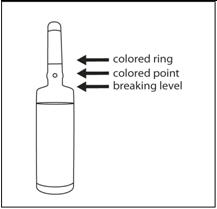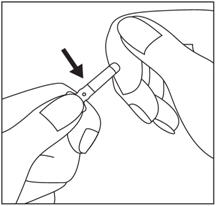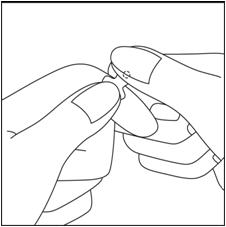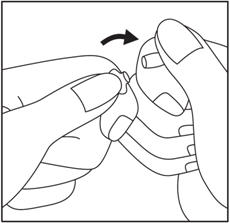 DRUG LABEL: Haloperidol
NDC: 64725-0911 | Form: INJECTION
Manufacturer: TYA Pharmaceuticals
Category: prescription | Type: HUMAN PRESCRIPTION DRUG LABEL
Date: 20130506

ACTIVE INGREDIENTS: Haloperidol 5 mg/1 mL
INACTIVE INGREDIENTS: LACTIC ACID

HALOPERIDOL INJECTION (FOR IMMEDIATE RELEASE)

WARNING

Increased Mortality in Elderly Patients with Dementia-Related Psychosis

Elderly patients with dementia-related psychosis treated with antipsychotic drugs are at an increased risk of death. Analyses of seventeen placebo-controlled trials (modal duration of 10 weeks), largely in patients taking atypical antipsychotic drugs, revealed a risk of death in drug-treated patients of between 1.6 to 1.7 times the risk of death in placebo-treated patients. Over the course of a typical 10-week controlled trial, the rate of death in drug-treated patients was about 4.5%, compared to a rate of about 2.6% in the placebo group. Although the causes of death were varied, most of the deaths appeared to be either cardiovascular (e.g., heart failure, sudden death) or infectious (e.g., pneumonia) in nature. Observational studies suggest that, similar to atypical antipsychotic drugs, treatment with conventional antipsychotic drugs may increase mortality. The extent to which the findings of increased mortality in observational studies may be attributed to the antipsychotic drug as opposed to some characteristic(s) of the patients is not clear. Haloperidol Injection is not approved for the treatment of patients with dementia-related psychosis (see). WARNINGS

DESCRIPTION

Haloperidol is the first of the butyrophenone series of major antipsychotics. The chemical designation is 4-[4-(p-chlorophenyl)-4-hydroxypiperidino]-4'-fluorobutyrophenone and it has the following structural formula:

Haloperidol is available as a sterile parenteral form for intramuscular injection. The injection provides 5 mg haloperidol (as the lactate) and lactic acid for pH adjustment between 3.0 – 3.6.

ACTIONS

The precise mechanism of action has not been clearly established.

INDICATIONS

Haloperidol is indicated for use in the treatment of schizophrenia.

Haloperidol is indicated for the control of tics and vocal utterances of Tourette's Disorder.

CONTRAINDICATIONS

Haloperidol is contraindicated in severe toxic central nervous system depression or comatose states from any cause and in individuals who are hypersensitive to this drug or have Parkinson's disease.

WARNINGS

Increased Mortality in Elderly Patients with Dementia-Related Psychosis

Elderly patients with dementia-related psychosis treated with antipsychotic drugs are at an increased risk of death. Haloperidol Injection is not approved for the treatment of patients with dementia-related psychosis (see). BOXED WARNING

Cardiovascular Effects

Cases of sudden death, QT-prolongation, and Torsades de Pointes have been reported in patients receiving haloperidol. Higher than recommended doses of any formulation and intravenous administration of haloperidol appear to be associated with a higher risk of QT-prolongation and Torsades de Pointes. Although cases have been reported even in the absence of predisposing factors, particular caution is advised in treating patients with other QT-prolonging conditions (including electrolyte imbalance [particularly hypokalemia and hypomagnesemia], drugs known to prolong QT, underlying cardiac abnormalities, hypothyroidism, and familial long QT-syndrome). HALOPERIDOL INJECTION IS NOT APPROVED FOR INTRAVENOUS ADMINISTRATION. If HALOPERIDOL is administered intravenously, the ECG should be monitored for QT prolongation and arrhythmias.

Tardive Dyskinesia

A syndrome consisting of potentially irreversible, involuntary, dyskinetic movements may develop in patients treated with antipsychotic drugs. Although the prevalence of the syndrome appears to be highest among the elderly, especially elderly women, it is impossible to rely upon prevalence estimates to predict, at the inception of antipsychotic treatment, which patients are likely to develop the syndrome. Whether antipsychotic drug products differ in their potential to cause tardive dyskinesia is unknown.

Both the risk of developing tardive dyskinesia and the likelihood that it will become irreversible are believed to increase as the duration of treatment and the total cumulative dose of antipsychotic drugs administered to the patient increase. However, the syndrome can develop, although much less commonly, after relatively brief treatment periods at low doses.

There is no known treatment for established cases of tardive dyskinesia, although the syndrome may remit, partially or completely, if antipsychotic treatment is withdrawn. Antipsychotic treatment, itself, however, may suppress (or partially suppress) the signs and symptoms of the syndrome and thereby may possibly mask the underlying process. The effect that symptomatic suppression has upon the long-term course of the syndrome is unknown.

Given these considerations, antipsychotic drugs should be prescribed in a manner that is most likely to minimize the occurrence of tardive dyskinesia. Chronic antipsychotic treatment should generally be reserved for patients who suffer from a chronic illness that, 1) is known to respond to antipsychotic drugs, and, 2) for whom alternative, equally effective, but potentially less harmful treatments are available or appropriate. In patients who do require chronic treatment, the smallest dose and the shortest duration of treatment producing a satisfactory clinical response should be sought. The need for continued treatment should be reassessed periodically. not

If signs and symptoms of tardive dyskinesia appear in a patient on antipsychotics, drug discontinuation should be considered. However, some patients may require treatment despite the presence of the syndrome.

(For further information about the description of tardive dyskinesia and its clinical detection, please refer to .) ADVERSE REACTIONS

Neuroleptic Malignant Syndrome (NMS)

A potentially fatal symptom complex sometimes referred to as Neuroleptic Malignant Syndrome (NMS) has been reported in association with antipsychotic drugs. Clinical manifestations of NMS are hyperpyrexia, muscle rigidity, altered mental status (including catatonic signs) and evidence of autonomic instability (irregular pulse or blood pressure, tachycardia, diaphoresis, and cardiac dysrhythmias). Additional signs may include elevated creatine phosphokinase, myoglobinuria (rhabdomyolysis) and acute renal failure.

The diagnostic evaluation of patients with this syndrome is complicated. In arriving at a diagnosis, it is important to identify cases where the clinical presentation includes both serious medical illness (e.g., pneumonia, systemic infection, etc.) and untreated or inadequately treated extrapyramidal signs and symptoms (EPS). Other important considerations in the differential diagnosis include central anticholinergic toxicity, heat stroke, drug fever and primary central nervous system (CNS) pathology.

The management of NMS should include 1) immediate discontinuation of antipsychotic drugs and other drugs not essential to concurrent therapy, 2) intensive symptomatic treatment and medical monitoring, and 3) treatment of any concomitant serious medical problems for which specific treatments are available. There is no general agreement about specific pharmacological treatment regimens for uncomplicated NMS.

If a patient requires antipsychotic drug treatment after recovery from NMS, the potential reintroduction of drug therapy should be carefully considered. The patient should be carefully monitored, since recurrences of NMS have been reported.

Hyperpyrexia and heat stroke, not associated with the above symptom complex, have also been reported with haloperidol.

Usage in Pregnancy

Rodents given 2 to 20 times the usual maximum human dose of haloperidol by oral or parenteral routes showed an increase in incidence of resorption, reduced fertility, delayed delivery and pup mortality. No teratogenic effect has been reported in rats, rabbits or dogs at dosages within this range, but cleft palate has been observed in mice given 15 times the usual maximum human dose. Cleft palate in mice appears to be a nonspecific response to stress or nutritional imbalance as well as to a variety of drugs, and there is no evidence to relate this phenomenon to predictable human risk for most of these agents.

There are no well controlled studies with haloperidol in pregnant women. There are reports, however, of cases of limb malformations observed following maternal use of haloperidol along with other drugs which have suspected teratogenic potential during the first trimester of pregnancy. Causal relationships were not established in these cases. Since such experience does not exclude the possibility of fetal damage due to haloperidol, this drug should be used during pregnancy or in women likely to become pregnant only if the benefit clearly justifies a potential risk to the fetus. Infants should not be nursed during drug treatment.

Non-teratogenic Effects

Neonates exposed to antipsychotic drugs (including haloperidol) during the third trimester of pregnancy are at risk for extrapyramidal and/or withdrawal symptoms following delivery. There have been reports of agitation, hypertonia, hypotonia, tremor, somnolence, respiratory distress, and feeding disorder in these neonates. These complications have varied in severity; while in some cases symptoms have been self-limited, in other cases neonates have required intensive care unit support and prolonged hospitalization.

Haloperidol should be used during pregnancy only if the potential benefit justifies the potential risk to the fetus.

Combined Use of Haloperidol and Lithium

An encephalopathic syndrome (characterized by weakness, lethargy, fever, tremulousness and confusion, extrapyramidal symptoms, leukocytosis, elevated serum enzymes, BUN, and FBS) followed by irreversible brain damage has occurred in a few patients treated with lithium plus haloperidol. A causal relationship between these events and the concomitant administration of lithium and haloperidol has not been established; however, patients receiving such combined therapy should be monitored closely for early evidence of neurological toxicity and treatment discontinued promptly if such signs appear.

General

A number of cases of bronchopneumonia, some fatal, have followed the use of antipsychotic drugs, including haloperidol. It has been postulated that lethargy and decreased sensation of thirst due to central inhibition may lead to dehydration, hemoconcentration and reduced pulmonary ventilation. Therefore, if the above signs and symptoms appear, especially in the elderly, the physician should institute remedial therapy promptly.

Although not reported with haloperidol, decreased serum cholesterol and/or cutaneous and ocular changes have been reported in patients receiving chemically-related drugs.

Haloperidol may impair the mental and/or physical abilities required for the performance of hazardous tasks such as operating machinery or driving a motor vehicle. The ambulatory patient should be warned accordingly.

The use of alcohol with this drug should be avoided due to possible additive effects and hypotension.

PRECAUTIONS

Leukopenia, Neutropenia, and Agranulocytosis

Class Effect

In clinical trial and/or postmarketing experience, events of leukopenia/neutropenia have been reported temporally related to antipsychotic agents, including haloperidol. Agranulocytosis has also been reported.

Possible risk factors for leukopenia/neutropenia include pre-existing low white blood cell count (WBC) and history of drug-induced leukopenia/neutropenia. Patients with a history of a clinically significant low WBC or a drug-induced leukopenia/neutropenia should have their complete blood count (CBC) monitored frequently during the first few months of therapy and discontinuation of haloperidol should be considered at the first sign of a clinically significant decline in WBC in the absence of other causative factors.

Patients with clinically significant neutropenia should be carefully monitored for fever or other symptoms or signs of infection and treated promptly if such symptoms or signs occur. Patients with severe neutropenia (absolute neutrophil count <1000/mm) should discontinue haloperidol and have their WBC followed until recovery.^3

Other

Haloperidol should be administered cautiously to patients:

- with severe cardiovascular disorders, because of the possibility of transient hypotension and/or precipitation of anginal pain. Should hypotension occur and a vasopressor be required, epinephrine should not be used since haloperidol may block its vasopressor activity and paradoxical further lowering of the blood pressure may occur. Instead, metaraminol, phenylephrine or norepinephrine should be used.
- receiving anticonvulsant medications, with a history of seizures, or with EEG abnormalities, because haloperidol may lower the convulsive threshold. If indicated, adequate anticonvulsant therapy should be concomitantly maintained.
- with known allergies, or with a history of allergic reactions to drugs.
- receiving anticoagulants, since an isolated instance of interference occurred with the effects of one anticoagulant (phenindione).

If concomitant antiparkinson medication is required, it may have to be continued after haloperidol is discontinued because of the difference in excretion rates. If both are discontinued simultaneously, extrapyramidal symptoms may occur. The physician should keep in mind the possible increase in intraocular pressure when anticholinergic drugs, including antiparkinson agents, are administered concomitantly with haloperidol.

As with other antipsychotic agents, it should be noted that haloperidol may be capable of potentiating CNS depressants such as anesthetics, opiates, and alcohol.

In a study of 12 schizophrenic patients coadministered haloperidol and rifampin, plasma haloperidol levels were decreased by a mean of 70% and mean scores on the Brief Psychiatric Rating Scale were increased from baseline. In 5 other schizophrenic patients treated with haloperidol and rifampin, discontinuation of rifampin produced a mean 3.3-fold increase in haloperidol concentrations. Thus, careful monitoring of clinical status is warranted when rifampin is administered or discontinued in haloperidol-treated patients.

When haloperidol is used to control mania in cyclic disorders, there may be a rapid mood swing to depression.

Severe neurotoxicity (rigidity, inability to walk or talk) may occur in patients with thyrotoxicosis who are also receiving antipsychotic medication, including haloperidol.

No mutagenic potential of haloperidol was found in the Ames Salmonella microsomal activation assay. Negative or inconsistent positive findings have been obtained in and studies of effects of haloperidol on chromosome structure and number. The available cytogenetic evidence is considered too inconsistent to be conclusive at this time. in vitroin vivo

Carcinogenicity studies using oral haloperidol were conducted in Wistar rats (dosed at up to 5 mg/kg daily for 24 months) and in Albino Swiss mice (dosed at up to 5 mg/kg daily for 18 months). In the rat study survival was less than optimal in all dose groups, reducing the number of rats at risk for developing tumors. However, although a relatively greater number of rats survived to the end of the study in high-dose male and female groups, these animals did not have a greater incidence of tumors than control animals. Therefore, although not optimal, this study does suggest the absence of a haloperidol related increase in the incidence of neoplasia in rats at doses up to 20 times the usual daily human dose for chronic or resistant patients.

In female mice at 5 and 20 times the highest initial daily dose for chronic or resistant patients, there was a statistically significant increase in mammary gland neoplasia and total tumor incidence; at 20 times the same daily dose there was a statistically significant increase in pituitary gland neoplasia. In male mice, no statistically significant differences in incidences of total tumors or specific tumor types were noted.

Antipsychotic drugs elevate prolactin levels; the elevation persists during chronic administration. Tissue culture experiments indicate that approximately one-third of human breast cancers are prolactin dependent , a factor of potential importance if the prescription of these drugs is contemplated in a patient with a previously detected breast cancer. Although disturbances such as galactorrhea, amenorrhea, gynecomastia, and impotence have been reported, the clinical significance of elevated serum prolactin levels is unknown for most patients. An increase in mammary neoplasms has been found in rodents after chronic administration of antipsychotic drugs. Neither clinical studies nor epidemiologic studies conducted to date, however, have shown an association between chronic administration of these drugs and mammary tumorigenesis; the available evidence is considered too limited to be conclusive at this time. in vitro

There are no well controlled studies with haloperidol in pregnant women. There are reports, however, of cases of limb malformations observed following maternal use of haloperidol along with other drugs which have suspected teratogenic potential during the first trimester of pregnancy. Causal relationships were not established in these cases. Since such experience does not exclude the possibility of fetal damage due to haloperidol, this drug should be used during pregnancy or in women likely to become pregnant only if the benefit clearly justifies a potential risk to the fetus. Infants should not be nursed during drug treatment.

Pediatric Use

Safety and effectiveness in pediatric patients have not been established.

Geriatric Use

Clinical studies of haloperidol did not include sufficient numbers of subjects aged 65 and over to determine whether they respond differently from younger subjects. Other reported clinical experience has not consistently identified differences in responses between the elderly and younger patients. However, the prevalence of tardive dyskinesia appears to be highest among the elderly, especially elderly women (see). Also, the pharmacokinetics of haloperidol in geriatric patients generally warrants the use of lower doses (see). WARNINGS, Tardive Dyskinesia DOSAGE AND ADMINISTRATION

ADVERSE REACTIONS

Cardiovascular Effects

Tachycardia, hypotension, and hypertension have been reported. QT prolongation and/or ventricular arrhythmias have also been reported, in addition to ECG pattern changes compatible with the polymorphous configuration of torsade de pointes, and may occur more frequently with high doses and in predisposed patients (see and). WARNINGSPRECAUTIONS

Cases of sudden and unexpected death have been reported in association with the administration of haloperidol. The nature of the evidence makes it impossible to determine definitively what role, if any, haloperidol played in the outcome of the reported cases. The possibility that haloperidol caused death cannot, of course, be excluded, but it is to be kept in mind that sudden and unexpected death may occur in psychotic patients when they go untreated or when they are treated with other antipsychotic drugs.

CNS Effects

Extrapyramidal Symptoms (EPS)

EPS during the administration of haloperidol have been reported frequently, often during the first few days of treatment. EPS can be categorized generally as Parkinson-like symptoms, akathisia, or dystonia (including opisthotonos and oculogyric crisis). While all can occur at relatively low doses, they occur more frequently and with greater severity at higher doses. The symptoms may be controlled with dose reductions or administration of antiparkinson drugs such as benztropine mesylate USP or trihexyphenidyl hydrochloride USP. It should be noted that persistent EPS have been reported; the drug may have to be discontinued in such cases.

Dystonia

Class Effect

Symptoms of dystonia, prolonged abnormal contractions of muscle groups, may occur in susceptible individuals during the first few days of treatment. Dystonic symptoms include: spasm of the neck muscles, sometimes progressing to tightness of the throat, swallowing difficulty, difficulty breathing, and/or protrusion of the tongue. While these symptoms can occur at low doses, they occur more frequently and with greater severity with high potency and at higher doses of first generation antipsychotic drugs. An elevated risk of acute dystonia is observed in males and younger age groups.

Withdrawal Emergent Neurological Signs

Generally, patients receiving short-term therapy experience no problems with abrupt discontinuation of antipsychotic drugs. However, some patients on maintenance treatment experience transient dyskinetic signs after abrupt withdrawal. In certain of these cases the dyskinetic movements are indistinguishable from the syndrome described below under "Tardive Dyskinesia" except for duration. It is not known whether gradual withdrawal of antipsychotic drugs will reduce the rate of occurrence of withdrawal emergent neurological signs but until further evidence becomes available, it seems reasonable to gradually withdraw use of haloperidol.

Tardive Dyskinesia

As with all antipsychotic agents haloperidol has been associated with persistent dyskinesias. Tardive dyskinesia, a syndrome consisting of potentially irreversible, involuntary, dyskinetic movements, may appear in some patients on long-term therapy or may occur after drug therapy has been discontinued. The risk appears to be greater in elderly patients on high-dose therapy, especially females. The symptoms are persistent and in some patients appear irreversible. The syndrome is characterized by rhythmical involuntary movements of tongue, face, mouth or jaw (e.g., protrusion of tongue, puffing of cheeks, puckering of mouth, chewing movements). Sometimes these may be accompanied by involuntary movements of extremities and the trunk.

There is no known effective treatment for tardive dyskinesia; antiparkinson agents usually do not alleviate the symptoms of this syndrome. It is suggested that all antipsychotic agents be discontinued if these symptoms appear. Should it be necessary to reinstitute treatment, or increase the dosage of the agent, or switch to a different antipsychotic agent, this syndrome may be masked.

It has been reported that fine vermicular movement of the tongue may be an early sign of tardive dyskinesia and if the medication is stopped at that time the full syndrome may not develop.

Tardive Dystonia

Tardive dystonia, not associated with the above syndrome, has also been reported. Tardive dystonia is characterized by delayed onset of choreic or dystonic movements, is often persistent, and has the potential of becoming irreversible.

Other CNS Effects

Insomnia, restlessness, anxiety, euphoria, agitation, drowsiness, depression, lethargy, headache, confusion, vertigo, grand mal seizures, exacerbation of psychotic symptoms including hallucinations, and catatonic-like behavioral states which may be responsive to drug withdrawal and/or treatment with anticholinergic drugs.

Body as a Whole

Neuroleptic malignant syndrome (NMS), hyperpyrexia and heat stroke have been reported with haloperidol. (See for further information concerning NMS.) WARNINGS

Hematologic Effects

Reports have appeared citing the occurrence of mild and usually transient leukopenia and leukocytosis, minimal decreases in red blood cell counts, anemia, or a tendency toward lymphomonocytosis. Agranulocytosis has rarely been reported to have occurred with the use of haloperidol, and then only in association with other medication.

Liver Effects

Impaired liver function and/or jaundice have been reported.

Dermatologic Reactions

Maculopapular and acneiform skin reactions and isolated cases of photosensitivity and loss of hair.

Endocrine Disorders

Lactation, breast engorgement, mastalgia, menstrual irregularities, gynecomastia, impotence, increased libido, hyperglycemia, hypoglycemia and hyponatremia.

Gastrointestinal Effects

Anorexia, constipation, diarrhea, hypersalivation, dyspepsia, nausea and vomiting.

Autonomic Reactions

Dry mouth, blurred vision, urinary retention, diaphoresis and priapism.

Respiratory Effects

Laryngospasm, bronchospasm and increased depth of respiration.

Special Senses

Cataracts, retinopathy and visual disturbances.

Postmarketing Events

Hyperammonemia has been reported in a 5½ year old child with citrullinemia, an inherited disorder of ammonia excretion, following treatment with haloperidol.

OVERDOSAGE

Manifestations

In general, the symptoms of overdosage would be an exaggeration of known pharmacologic effects and adverse reactions, the most prominent of which would be: 1) severe extrapyramidal reactions, 2) hypotension, or 3) sedation. The patient would appear comatose with respiratory depression and hypotension which could be severe enough to produce a shock-like state. The extrapyramidal reaction would be manifest by muscular weakness or rigidity and a generalized or localized tremor as demonstrated by the akinetic or agitans types respectively. With accidental overdosage, hypertension rather than hypotension occurred in a two-year old child. The risk of ECG changes associated with torsade de pointes should be considered. (For further information regarding torsade de pointes, please refer to .) ADVERSE REACTIONS

Treatment

Since there is no specific antidote, treatment is primarily supportive. A patent airway must be established by use of an oropharyngeal airway or endotracheal tube or, in prolonged cases of coma, by tracheostomy. Respiratory depression may be counteracted by artificial respiration and mechanical respirators. Hypotension and circulatory collapse may be counteracted by use of intravenous fluids, plasma, or concentrated albumin, and vasopressor agents such as metaraminol, phenylephrine and norepinephrine. Epinephrine should not be used. In case of severe extrapyramidal reactions, antiparkinson medication should be administered. ECG and vital signs should be monitored especially for signs of Q-T prolongation or dysrhythmias and monitoring should continue until the ECG is normal. Severe arrhythmias should be treated with appropriate anti-arrhythmic measures.

DOSAGE AND ADMINISTRATION

There is considerable variation from patient to patient in the amount of medication required for treatment. As with all drugs used to treat schizophrenia, dosage should be individualized according to the needs and response of each patient. Dosage adjustments, either upward or downward, should be carried out as rapidly as practicable to achieve optimum therapeutic control.

To determine the initial dosage, consideration should be given to the patient's age, severity of illness, previous response to other antipsychotic drugs, and any concomitant medication or disease state. Debilitated or geriatric patients, as well as those with a history of adverse reactions to antipsychotic drugs, may require less haloperidol. The optimal response in such patients is usually obtained with more gradual dosage adjustments and at lower dosage levels.

Parenteral medication, administered intramuscularly in doses of 2 to 5 mg, is utilized for prompt control of the acutely agitated schizophrenic patient with moderately severe to very severe symptoms. Depending on the response of the patient, subsequent doses may be given, administered as often as every hour, although 4 to 8 hour intervals may be satisfactory.

Controlled trials to establish the safety and effectiveness of intramuscular administration in children have not been conducted.

Parenteral drug products should be inspected visually for particulate matter and discoloration prior to administration, whenever solution and container permit.

Switchover Procedure

An oral form should supplant the injectable as soon as practicable. In the absence of bioavailability studies establishing bioequivalence between these two dosage forms the following guidelines for dosage are suggested. For an initial approximation of the total daily dose required, the parenteral dose administered in the preceding 24 hours may be used. Since this dose is only an initial estimate, it is recommended that careful monitoring of clinical signs and symptoms, including clinical efficacy, sedation, and adverse effects, be carried out periodically for the first several days following the initiation of switchover. In this way, dosage adjustments, either upward or downward, can be quickly accomplished. Depending on the patient's clinical status, the first oral dose should be given within 12–24 hours following the last parenteral dose.

Instructions for Opening Ampule

1. Medication often rests in the top part of the ampule. Before breaking the ampule, lightly tap the top of the ampule with your finger until all fluid moves to the bottom portion of the ampule. The ampule has a colored ring(s) and colored point which aids in the placement of fingers while breaking the ampule.

Step 1

2. Hold the ampule between thumb and index finger with the colored point facing you.

Step 2

3. Position the index finger of the other hand to support the neck of the ampule. Position the thumb so that it covers the colored point and is parallel to the colored ring(s).

Step 3

4. Keeping the thumb on the colored point and with the index fingers close together, apply firm pressure on the colored point in the direction of the arrow to snap the ampule open.

Step 4

HOW SUPPLIED

NDC:64725-0911-1 in a BOX of 10 INJECTIONS

STORAGE AND HANDLING

Store Haloperidol Injection at controlled room temperature (15°–30°C, 59°–86°F). Protect from light. Do not freeze.

Product of Belgium

Manufactured by: GlaxoSmithKline Manufacturing S.p.A. Parma, Italy

Manufactured for: Patriot Pharmaceuticals, LLC

Horsham, PA 19044

For more information, call 1-800-667-8570

©Patriot 2011

Issued September 2011